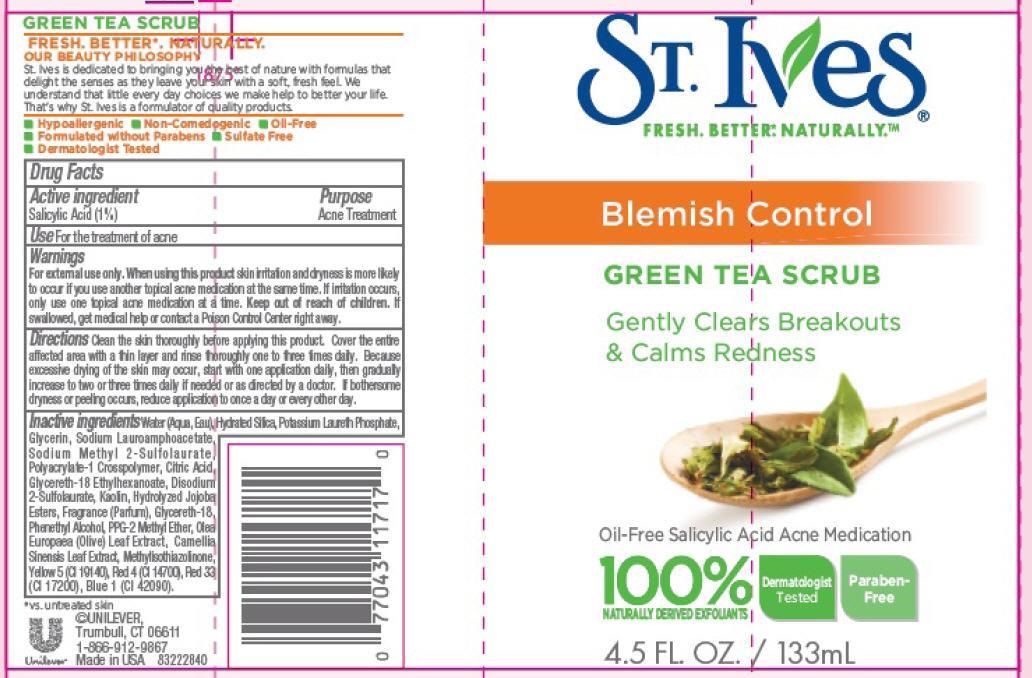 DRUG LABEL: St. Ives
NDC: 64942-1296 | Form: EMULSION
Manufacturer: CONOPCO Inc. d/b/a Unilever
Category: otc | Type: HUMAN OTC DRUG LABEL
Date: 20130430

ACTIVE INGREDIENTS: Salicylic Acid 0.01 g/1 mL
INACTIVE INGREDIENTS: WATER; HYDRATED SILICA; GLYCERIN; SODIUM LAUROAMPHOACETATE; SODIUM METHYL 2-SULFOLAURATE; CITRIC ACID MONOHYDRATE; GLYCERETH-18 ETHYLHEXANOATE; DISODIUM 2-SULFOLAURATE; KAOLIN; HYDROLYZED JOJOBA ESTERS (ACID FORM); GLYCERETH-18; PPG-2 METHYL ETHER; PHENYLETHYL ALCOHOL; OLEA EUROPAEA LEAF; METHYLISOTHIAZOLINONE; GREEN TEA LEAF; FD&C BLUE NO. 1; FD&C YELLOW NO. 5; D&C RED NO. 33; FD&C RED NO. 4

St. Ives Blemish Control Green Tea Scrub

Active ingredient
Salicylic Acid (1%)

Purpose
Acne Treatment

Use
For the treatment of acne

Warnings
For external use only.

When using this product skin irritation and dryness is more likely to occur if you use another topical acne medication at the same time. If irritation occurs, only use one topical acne medication at a time.

Keep out of reach of children. If swallowed, get medical help or contact a Poison Control Center right away.

DOSAGE AND ADMINISTRATION

Directions Clean the skin thoroughly before applying this product.Cover the entire affected area with a thin layer and rinse thoroughly one to three times daily. Because excessive drying of the skin may occur, start with one application daily, then gradually increase to two or three times daily if needed or as directed by a doctor. If bothersome dryness or peeling occurs, reduce application to once a day or every other day.

Inactive ingredients

Water (Aqua, Eau), Hydrated Silica, Potassium Laureth Phosphate, Glycerin, Sodium Lauroamphoacetate, Sodium Methyl 2-Sulfolaurate, Polyacrylate-1 Crosspolymer, Citric Acid, Glycereth-18 Ethylhexanoate, Disodium 2-Sulfolaurate, Kaolin, Hydrolyzed Jojoba Esters, Fragrance (Parfum), Glycereth-18, Phenethyl Alcohol, PPG-2 Methyl Ether, Olea Europaea (Olive) Leaf Extract, Camellia Sinensis Leaf Extract, Methylisothiazolinone, Yellow 5 (CI 19140), Red 4 (CI 14700), Red 33 (CI 17200), Blue 1 (CI 42090).

QUESTIONS

1-866-912-9867

PACKAGE LABEL

PDP